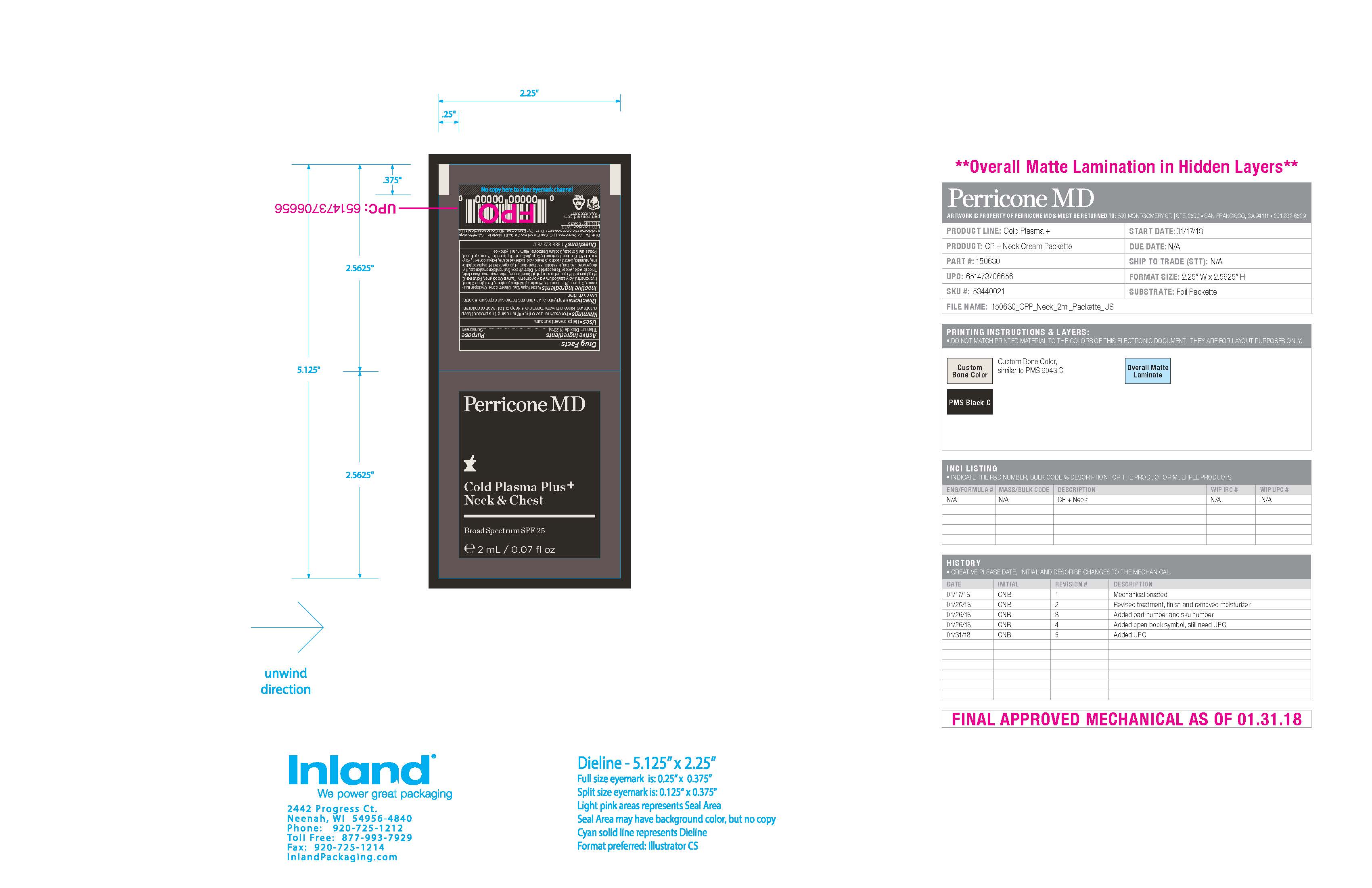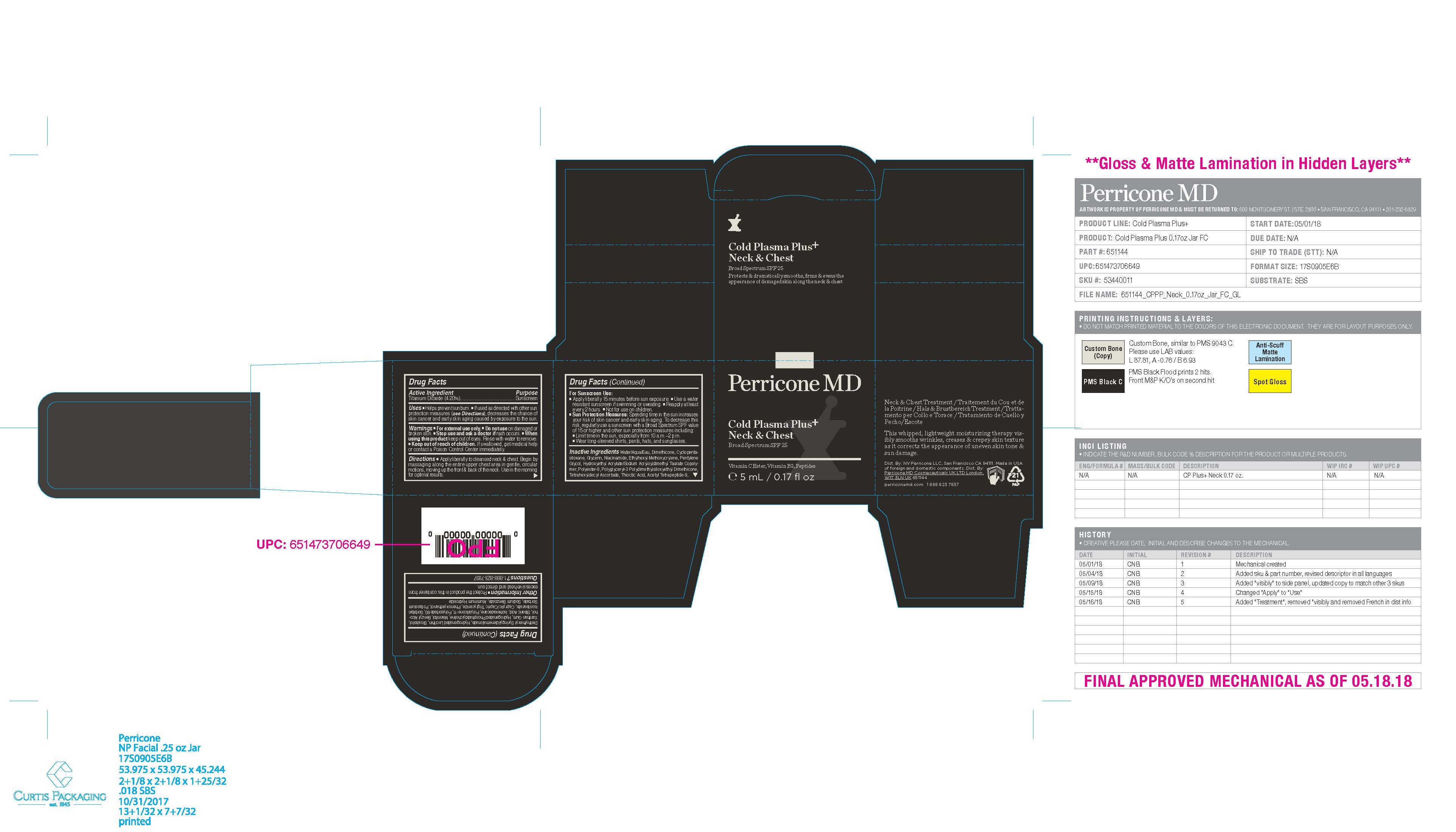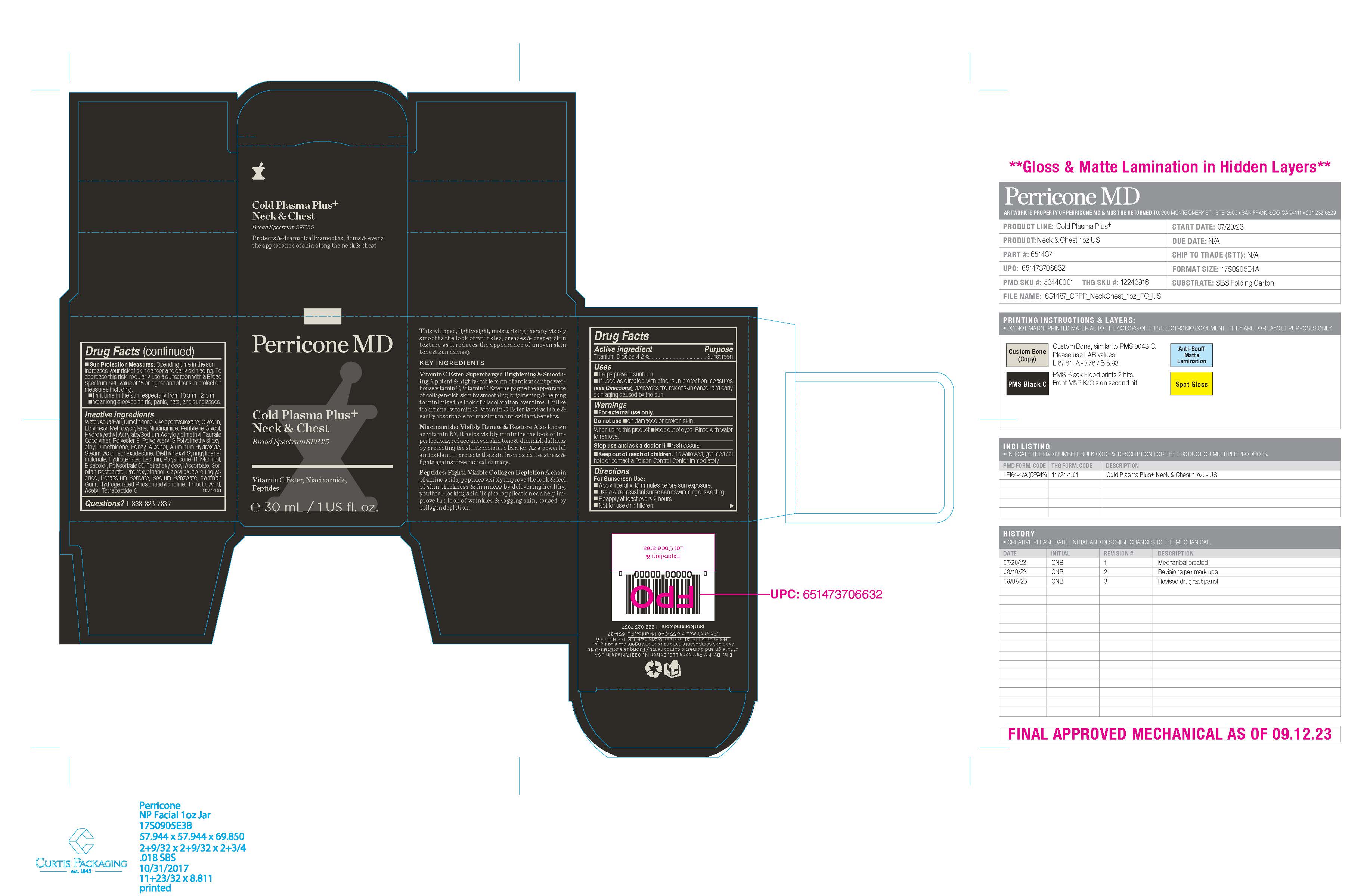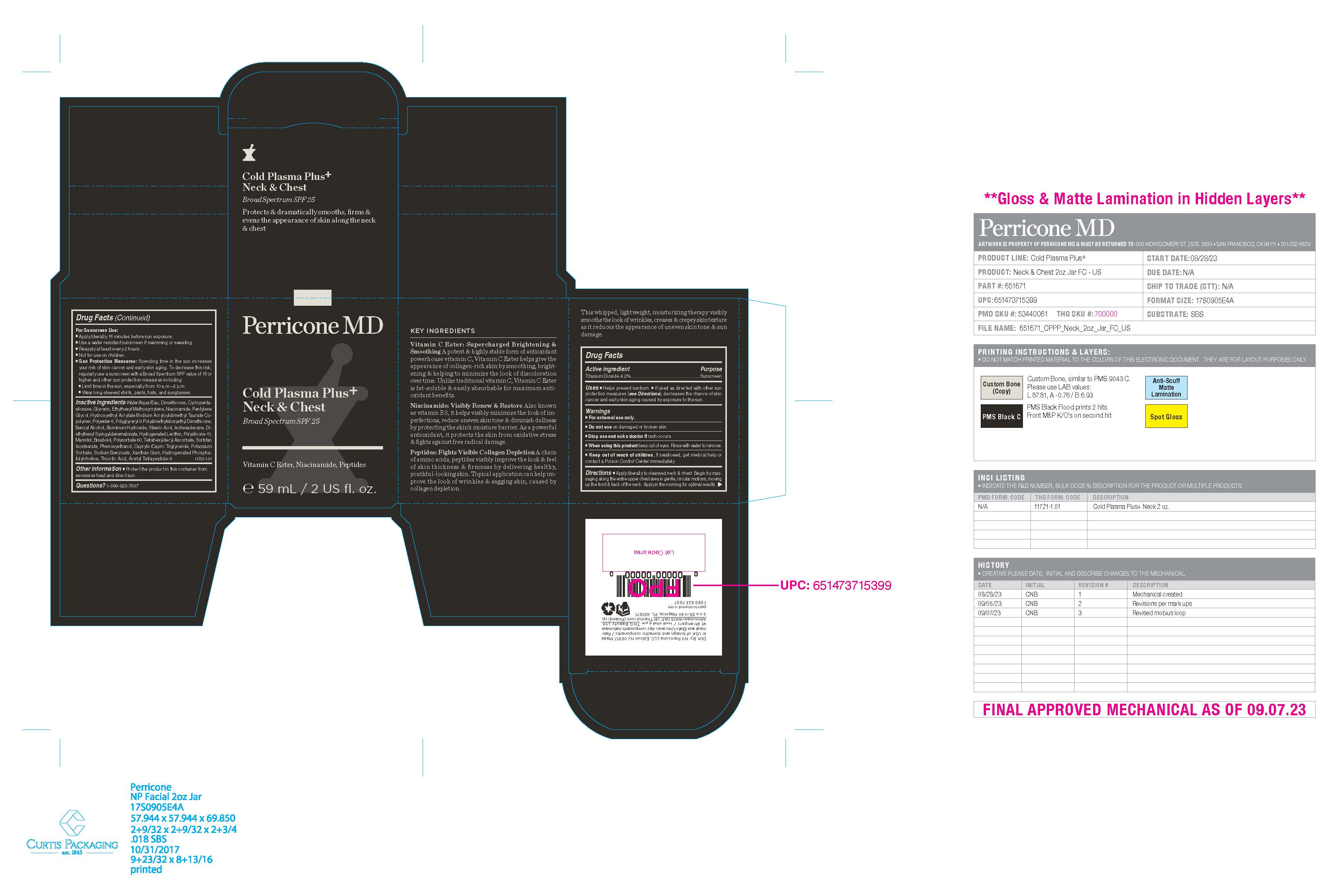 DRUG LABEL: Perricone MD Cold Plasma Plus Neck and Chest Broad Spectrum SPF 25
NDC: 84448-644 | Form: CREAM
Manufacturer: THG Beauty USA LLC
Category: otc | Type: HUMAN OTC DRUG LABEL
Date: 20251105

ACTIVE INGREDIENTS: TITANIUM DIOXIDE 4.2 g/100 mL
INACTIVE INGREDIENTS: XANTHAN GUM; MANNITOL; ISOHEXADECANE; BENZYL ALCOHOL; ALUMINUM HYDROXIDE; STEARIC ACID; MEDIUM-CHAIN TRIGLYCERIDES; ETHYLHEXYL METHOXYCRYLENE; PENTYLENE GLYCOL; HYDROXYETHYL ACRYLATE/SODIUM ACRYLOYLDIMETHYL TAURATE COPOLYMER (45000 MPA.S AT 1%); DIMETHICONE/VINYL DIMETHICONE CROSSPOLYMER (SOFT PARTICLE); GLYCERIN; NIACINAMIDE; POLYGLYCERYL-3 POLYDIMETHYLSILOXYETHYL DIMETHICONE (4000 MPA.S); DIETHYLHEXYL SYRINGYLIDENEMALONATE; POTASSIUM SORBATE; DIMETHICONE; WATER; TETRAHEXYLDECYL ASCORBATE; THIOCTIC ACID; ACETYL TETRAPEPTIDE-9; CYCLOMETHICONE 5; POLYESTER-8 (1400 MW, CYANODIPHENYLPROPENOYL CAPPED); LEVOMENOL; HYDROGENATED SOYBEAN LECITHIN; POLYSORBATE 60; SORBITAN ISOSTEARATE; PHENOXYETHANOL; HYDROGENATED SOYBEAN PHOSPHATIDYLCHOLINE; SODIUM BENZOATE

ACTIVE INGREDIENT

Titanium Dioxide 4.2%

INDICATIONS AND USAGE

■ Helps prevent sunburn. ■ If used as directed with other sun protection measures (see Directions), decreases the chance of skin
cancer and early skin aging caused by exposure to the sun.

WARNINGS

■ For external use only.

■ Do not use on damaged or broken skin.

■ Stop use and ask a doctor if rash occurs.

■ When using this product keep out of eyes. Rinse with water to remove.

■ Keep out of reach of children. If swallowed, get medical help or contact a Poison Control Center immediately.

DOSAGE AND ADMINISTRATION

■ Apply liberally to cleansed neck & chest. Begin by massaging along the entire upper chest area in gentle, circular motions, moving
up the front & back of the neck. Apply in the morning for optimal results

For Sunscreen Use:
■ Apply liberally 15 minutes before sun exposure.
■ Use a water resistant sunscreen if swimming or sweating.
■ Reapply at least every 2 hours.
■ Not for use on children.
■ Sun Protection Measures: Spending time in the sun increases your risk of skin cancer and early skin aging. To decrease this risk,
regularly use a sunscreen with a Broad Spectrum SPF value of 15 or higher and other sun protection measures including:
■ Limit time in the sun, especially from 10 a.m.–2 p.m.
■ Wear long-sleeved shirts, pants, hats, and sunglasses.

OTHER SAFETY INFORMATION

■ Protect the product in this container from excessive heat and direct sun.

INACTIVE INGREDIENT

Water/Aqua/Eau, Dimethicone, Cyclopentasiloxane, Glycerin, Ethylhexyl Methoxycrylene, Niacinamide, Pentylene Glycol, Hydroxyethyl Acrylate/Sodium Acryloyldimethyl Taurate Copolymer, Polyester-8, Polyglyceryl-3 Polydimethylsiloxyethyl Dimethicone,
Benzyl Alcohol, Aluminum Hydroxide, Stearic Acid, Isohexadecane, Diethylhexyl Syringylidenemalonate, Hydrogenated Lecithin, Polysilicone-11, Mannitol, Bisabolol, Polysorbate 60, Tetrahexyldecyl Ascorbate, Sorbitan Isostearate, Phenoxyethanol, Caprylic/Capric Triglyceride, Potassium Sorbate, Sodium Benzoate, Xanthan Gum, Hydrogenated Phosphatidylcholine, Thioctic Acid, Acetyl Tetrapeptide-9

QUESTIONS

1-888-823-7837